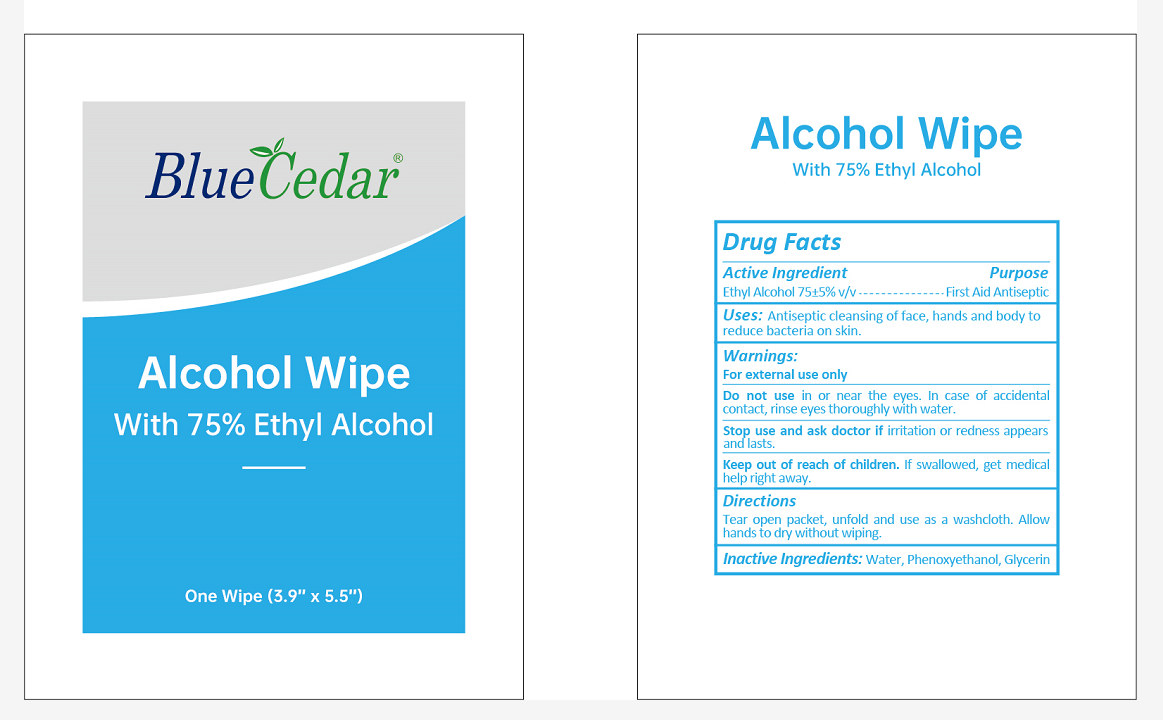 DRUG LABEL: Blue Cedar Alcohol Wipes
NDC: 55444-010 | Form: CLOTH
Manufacturer: Anhui Kiwi Biotech Co., Ltd.
Category: otc | Type: HUMAN OTC DRUG LABEL
Date: 20200701

ACTIVE INGREDIENTS: ALCOHOL 1.5 mL/1 1
INACTIVE INGREDIENTS: WATER; PHENOXYETHANOL; GLYCERIN

DOSAGE AND ADMINISTRATION

Store in a cool and dry place.

INACTIVE INGREDIENT

Water, Phenoxyethanol, Glycerin

INDICATIONS AND USAGE

open packet, unfold and use as a washcloth. Allow hands to dry without wiping.

ACTIVE INGREDIENT

Ethyl Alcohol

keep out of reach of children

PURPOSE

Disinfection
Sterilization
No Rinseing

WARNINGS

For external use only